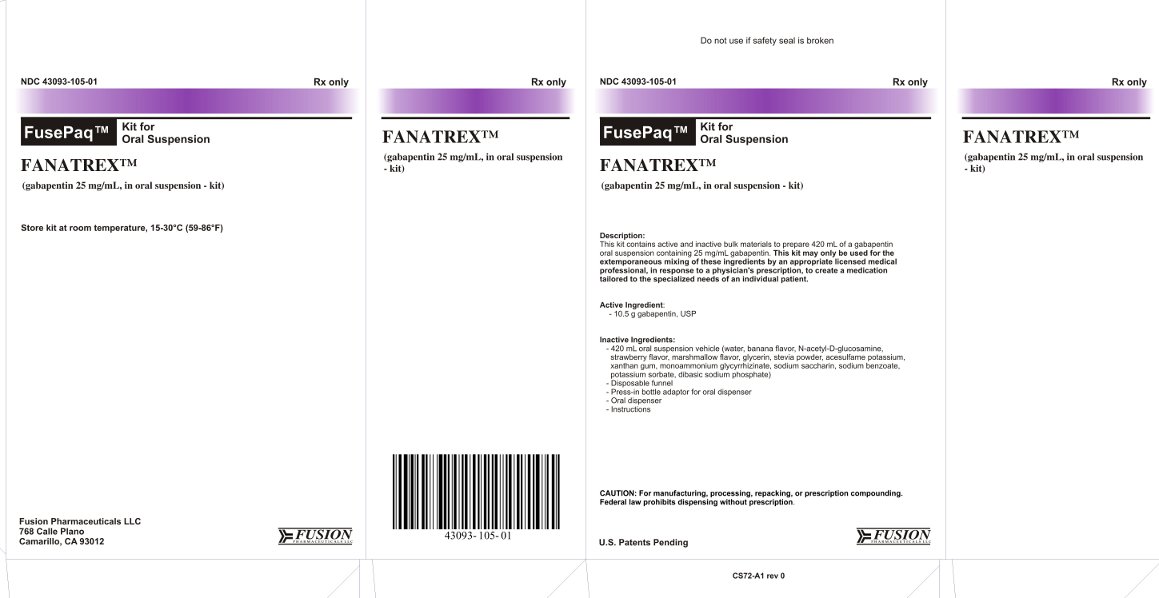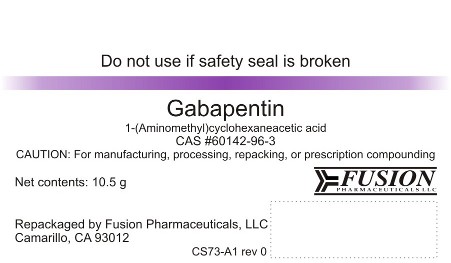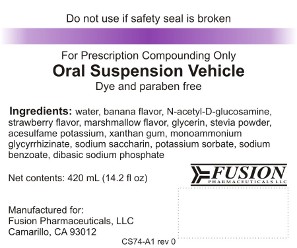 DRUG LABEL: Fanatrex
NDC: 43093-105 | Form: KIT | Route: ORAL
Manufacturer: California Pharmaceuticals LLC
Category: prescription | Type: HUMAN PRESCRIPTION DRUG LABEL
Date: 20151119

ACTIVE INGREDIENTS: GABAPENTIN 10.5 g/10.5 g
INACTIVE INGREDIENTS: WATER; BANANA; N-ACETYLGLUCOSAMINE; STRAWBERRY; ALTHAEA OFFICINALIS LEAF; GLYCERIN; STEVIA LEAF; ACESULFAME POTASSIUM; XANTHAN GUM; GLYCYRRHIZIN, AMMONIATED; SACCHARIN SODIUM; POTASSIUM SORBATE; SODIUM BENZOATE; SODIUM PHOSPHATE, DIBASIC

FANATREX

DESCRIPTION

NDC 43093-105-01
Rx only
FusePaq™
FANATREX™
(gabapentin 25 mg/mL, in oral suspension - kit)
FusePaq™ kits provide a convenient approach to rapidly prepare prescription medications, as all components are pre-measured. This kit is manufactured according to US FDA current Good Manufacturing Practices (cGMP).
Description:
This kit contains active and inactive bulk materials to prepare 420 mL of a gabapentin oral suspension containing 25 mg/mL gabapentin. This kit may only be used for the extemporaneous mixing of these ingredients by an appropriate licensed medical professional, in response to a physician's prescription, to create a medication tailored to the specialized needs of an individual patient.
Contents:

- 10.5 g gabapentin, USP
- 420 mL oral suspension vehicle (water, banana flavor, N-acetyl-D-glucosamine, strawberry flavor, marshmallow flavor, glycerin, stevia powder, acesulfame potassium, xanthan gum, monoammonium glycyrrhizinate, sodium saccharin, sodium benzoate, potassium sorbate, dibasic sodium phosphate)
- Disposable funnel
- Press-in bottle adaptor for oral dispenser
- Oral dispenser
- Instructions

SUGGESTED PREPARATION

Gabapentin, 25 mg/mL oral suspension

1 Remove and Inspect the Contents of the Kit
Remove kit contents. Ensure that seals are present and intact on the gabapentin and oral suspension vehicle bottles. If the seals are not intact, do not use the kit.

2 Prepare for Mixing
Wear gloves and eye protection during mixing operations. Remove the seal from the oral suspension bottle. Break the seal and remove the cap from the gabapentin bottle.

3 Transfer Gabapentin to the Suspension Bottle
Uncap the suspension bottle. Using the included funnel, carefully transfer the gabapentin powder to the suspension bottle. Cap the suspension bottle and mix thoroughly by inverting and shaking until all contents are dissolved. Uncap the suspension bottle. Pour a small amount of the mixed suspension back into the gabapentin bottle. Cap the gabapentin bottle and shake to ensure that all residual gabapentin has been dissolved. Pour the liquid through the funnel into the suspension bottle. Discard the funnel and gabapentin powder bottle.

4 Complete the Mixing Process
Insert the press-in bottle adaptor into the suspension bottle. Recap the suspension bottle. Mix well by inverting repeatedly several times. Visually ensure that all contents are dissolved.

5 Re-label the Suspension
Label the mixed suspension as required for prescription products. Ensure that the original oral suspension vehicle label is removed or obscured, since the original label is no longer accurate once the suspension is prepared.

Store the unused kit at room temperature of 15-30°C (59-86°F). Once prepared, store the mixed suspension between 15-30°C (59-86°F). The mixed suspension is stable for at least eight weeks, based upon real-time and accelerated stability studies.

Each lot of suspension vehicle is tested to meet microbial limits per USP Microbial Limit Test <61>. In addition, the suspension vehicle formulation has passed the USP <51> Antimicrobial Effectiveness Test.
An oral dispenser is provided in the kit and may be used to facilitate delivery of the suspension.

U.S. Patents Pending

Manufactured by:
Fusion Pharmaceuticals, LLC
768 Calle Plano
Camarillo, CA 93012

CS75-A1 rev 0

DRUG BOTTLE LABEL

Do not use if safety seal is broken
Gabapentin
1-(Aminomethyl)cyclohexaneacetic acid
CAS #60142-96-3
CAUTION: For manufacturing, processing, repacking, or prescription compounding
Net contents: 10.5 g
Repackaged by Fusion Pharmaceuticals, LLC
Camarillo, CA 93012
CS73-A1 rev 0

SUSPENSION BOTTLE LABEL

Do not use if safety seal is broken
For Prescription Compounding Only
Oral Suspension Vehicle
Dye and paraben free
Ingredients: water, banana flavor, N-acetyl-D-glucosamine, strawberry flavor, marshmallow flavor, glycerin, stevia powder, acesulfame potassium, xanthan gum, monoammonium glycyrrhizinate, sodium saccharin, potassium sorbate, sodium benzoate, dibasic sodium phosphate
Net Contents: 420 mL (14.2 fl oz)
Manufactured for:
Fusion Pharmaceuticals, LLC
Camarillo, CA 93012
CS74-A1 rev 0

Carton Box Label

Do not use if safety seal is broken
NDC 43093-105-01
Rx only
FusePaq™ Kit for Oral Suspension
Fanatrex™
(gabapentin 25 mg/mL, in oral suspension - kit)
Description:
This kit contains active and inactive bulk materials to prepare 420 mL of a gabapentin oral suspension containing 25 mg/mL gabapentin. This kit may only be used for the extemporaneous mixing of these ingredients by an appropriate licensed medical professional, in response to a physician's prescription, to create a medication tailored to the specialized needs of an individual patient.
Active Ingredient:

- 10.5 g gabapentin, USP

Inactive Ingredients:

- 420 mL oral suspension vehicle (water, banana flavor, N-acetyl-D-glucosamine, strawberry flavor, marshmallow flavor, glycerin, stevia powder, acesulfame potassium, xanthan gum, monoammonium glycyrrhizinate, sodium saccharin, potassium sorbate, sodium benzoate, dibasic sodium phosphate)
- Disposable funnel
- Press-in bottle adaptor for oral dispenser
- Oral dispenser
- Instructions

CAUTION: For manufacturing, processing, repacking, or presciption compounding. Federal law prohibits dispensing without prescription.
U.S. Patents Pending
CS72-A1 rev 0